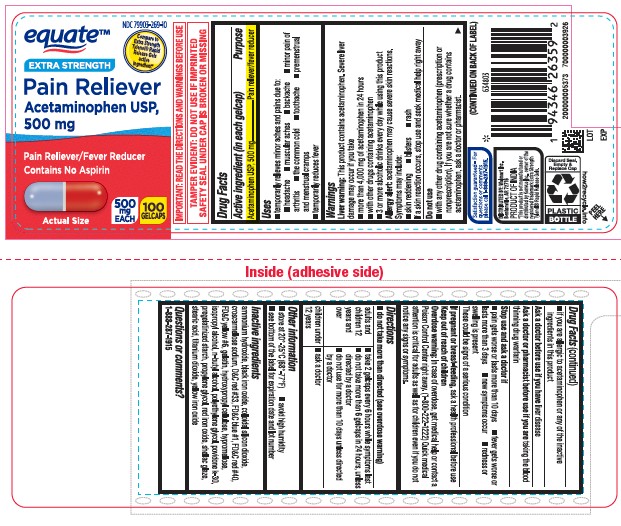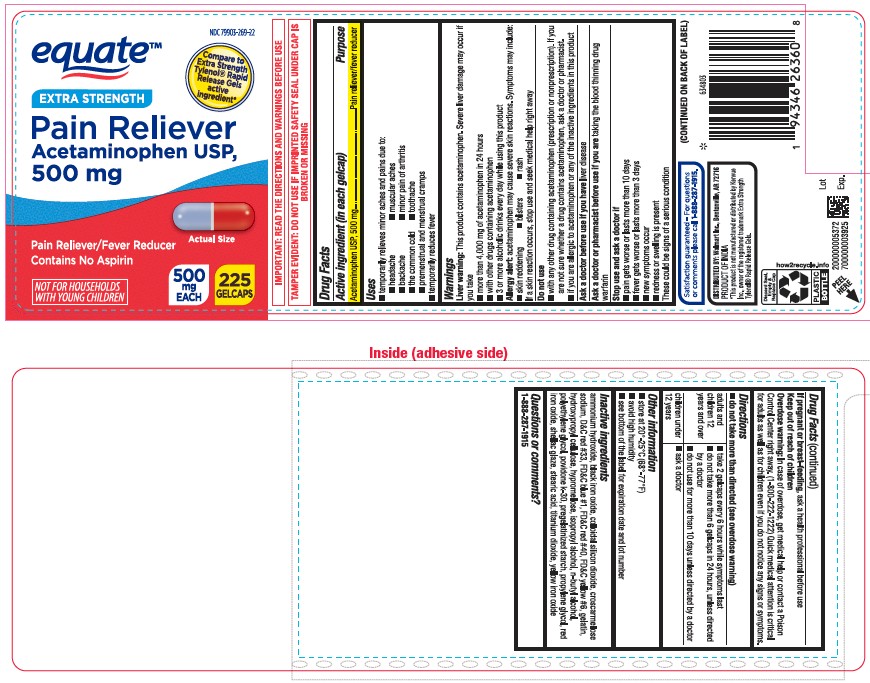 DRUG LABEL: Acetaminophen
NDC: 79903-269 | Form: TABLET
Manufacturer: Walmart
Category: otc | Type: HUMAN OTC DRUG LABEL
Date: 20251219

ACTIVE INGREDIENTS: ACETAMINOPHEN 500 mg/1 1
INACTIVE INGREDIENTS: AMMONIA; HYDROXYPROPYL CELLULOSE, UNSPECIFIED; CROSCARMELLOSE SODIUM; D&C RED NO. 33; FERROSOFERRIC OXIDE; GELATIN; HYPROMELLOSE, UNSPECIFIED; FERRIC OXIDE RED; BUTYL ALCOHOL; POLYETHYLENE GLYCOL, UNSPECIFIED; STARCH, CORN; PROPYLENE GLYCOL; POVIDONE K30; FD&C RED NO. 40; TITANIUM DIOXIDE; ISOPROPYL ALCOHOL; FD&C YELLOW NO. 6; SILICON DIOXIDE; FERRIC OXIDE YELLOW; SHELLAC; STEARIC ACID; FD&C BLUE NO. 1

Pain Reliever
Acetaminophen USP, 500 mg
Pain Reliever/Fever Reducer
Contains No Aspirin

Active ingredient (in each gelcap)

Acetaminophen USP, 500 mg

Purpose

Pain reliever/fever reducer

Uses

- temporarily relieves minor aches and pains due to:
- headache
- muscular aches
- backache
- minor pain of arthritis
- the common cold n toothache
- premenstrual and menstrual cramps
- temporarily reduces fever

Liver warning:

This product contains acetaminophen. Severe liverdamage may occur if you take

- more than 4,000mg of acetaminophen in 24 hours
- with other drugs containing acetaminophen
- 3 or more alcoholic drinks every day while using this product

Allergy alert:

acetaminophen may cause severe skin reactions. Symptoms may include:

- skin reddening
- blisters
- rash

If a skin reaction occurs, stop use and seekmedical help right away

Do not use

- with any other drug containing acetaminophen (prescription or nonprescription). If you are not sure whether a drug contains

acetaminophen, ask a doctor or pharmacist.

- if you are allergic to acetaminophen or any of the inactive ingredients in this product

Ask a doctor before use if you have

liver disease

Ask a doctor or pharmacist before use if you are

taking the blood thinning drug warfarin

Stop use and ask a doctor if

- pain gets worse or lasts more than 10 days
- fever gets worse or lasts more than 3 days
- new symptoms occur
- redness or swelling is present

These could be signs of a serious condition

If pregnant or breast-feeding,

ask a health professional before use

Keep out of reach of children

Overdose warning: In case of overdose, get medical help or contact a Poison Control Center right away. (1-800-222-1222) Quick medical attention is critical for adults as well as for children even if you do not notice any signs or symptoms.

Directions

- do not take more than directed (see overdose warning)

adults and children 12 years and over

- take 2 gelcaps every 6 hours while symptoms last
- do not take more than 6 gelcaps in 24 hours, unless directed by a doctor
- do not use for more than 10 days unless directed by a doctor

children under 12 years

- ask a doctor

Other information

- store at 20°-25°C (68°-77°F)
- avoid high humidity
- see bottom of the label for expiration date and lot number

Inactive ingredients

ammonium hydroxide, black iron oxide, colloidal silicon dioxide, croscarmellose sodium, D&C red #33, FD&C blue #1, FD&C red #40,
FD&C yellow #6, gelatin, hydroxypropyl cellulose, hypromellose, isopropyl alcohol, n-butyl alcohol, polyethylene glycol, povidone k-30,
pregelatinized starch, propylene glycol, red iron oxide, shellac glaze, stearic acid, titanium dioxide, yellow iron oxide

Questions or comments?

1-888-287-1915